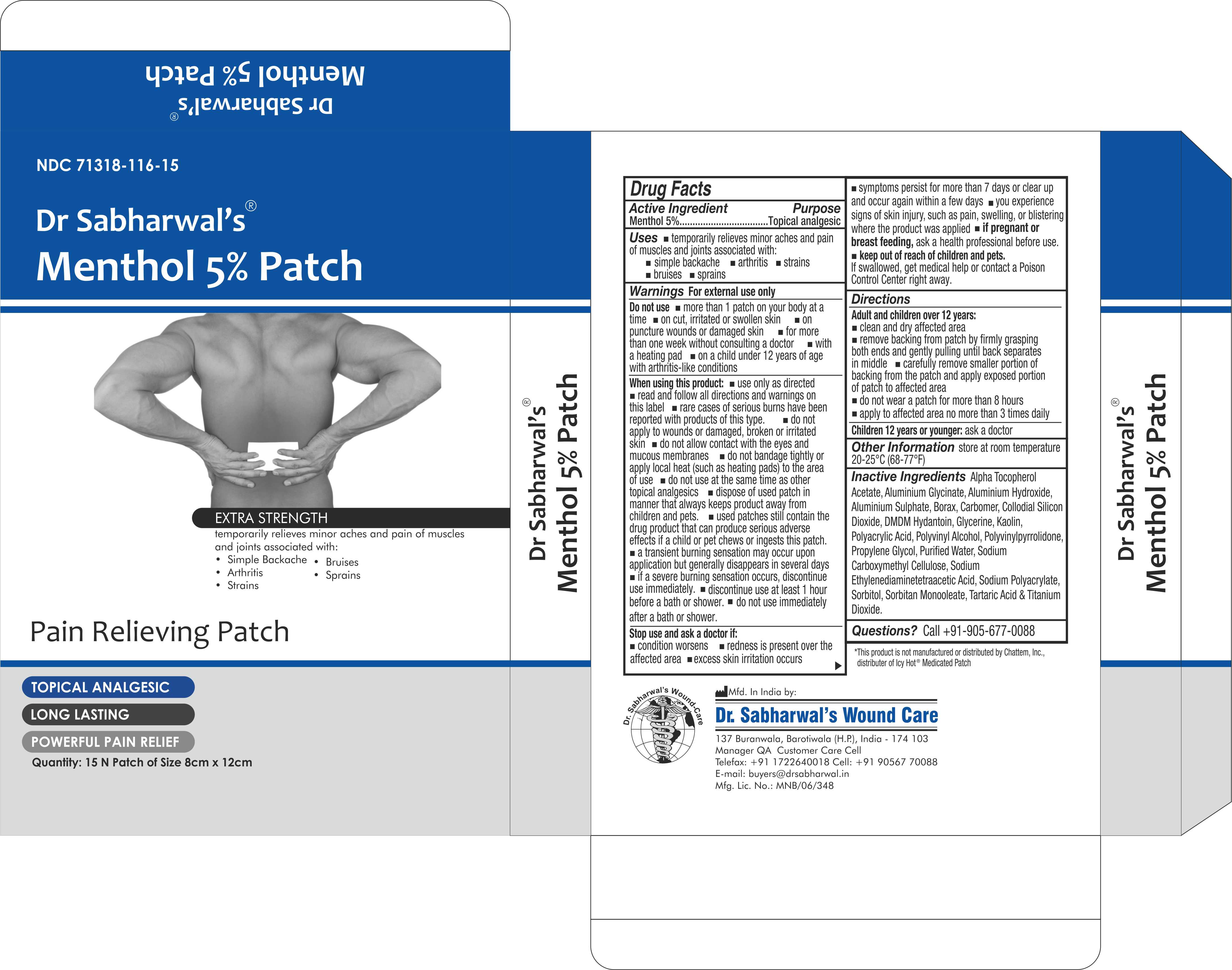 DRUG LABEL: Dr Sabharwals
NDC: 71318-116 | Form: PATCH
Manufacturer: Dr. Sabharwal's Wound Care
Category: otc | Type: HUMAN OTC DRUG LABEL
Date: 20260124

ACTIVE INGREDIENTS: MENTHOL 240 mg/1 1
INACTIVE INGREDIENTS: POVIDONE; PARAFFINUM LIQUIDUM; CARBOXYMETHYLCELLULOSE SODIUM; ALUMINIUM SULFATE OCTADECAHYDRATE; BORAX; PROPYLENE GLYCOL; DIHYDROXYALUMINUM AMINOACETATE; BUTYLATED HYDROXYTOLUENE; WATER; SODIUM POLYACRYLATE (8000 MW); SORBITAN MONOOLEATE; POLYACRYLIC ACID (250000 MW); TITANIUM DIOXIDE; ALUMINUM HYDROXIDE; POLYVINYL ALCOHOL (100000 MW); ALPHA-TOCOPHEROL ACETATE; TARTARIC ACID; KAOLIN; DMDM HYDANTOIN; GLYCERIN; EDETATE DISODIUM

ACTIVE INGREDIENT

Menthol 5%

PURPOSE

Topical Analgesic

INDICATIONS AND USAGE

Temporarily relieves minor aches and pain of muscles and joints accociated with, simple backache, arthritis, strains, bruises and sprains

WARNINGS

For external use only

DO NOT USE

- more than 1 patch on your body at a time
- on cut, irritated or swollen skin
- on puncture wounds or damaged skin
- for more than one week without consulting a doctor
- with heating pad
- on a child under 12 yeas of age with arthritis-like conditions

WHEN USING

- use only as directed.
- read and follow all directions and warnings on this label
- rare cases of serious burns have been reported with products of this type.
- do not apply to wounds or damaged, broken or irritated skin
- do not allow contact with eyes and mucous membranes
- do not bandage tightly or apply local heat (such as heating pads) to the area of use
- do not use at the same time as other topical analgesics
- dispose of used patch in manner that always keeps product away from children and pets
- used patches still contain the drug product that can produce serious adverse effects if a child or pet chews or ingests this patch
- a transient burning sensation may occur upon application but generally disappears in several days
- if a severe burning sensation occurs, discontinue use immediately.
- discontinue use at least 1 hour before a bath or shower.
- do not use immediately after a bath or shower.

ASK DOCTOR

- condition worsens
- redness is present over the affected area
- excess skin irritation occurs
- symptoms persist for more than 7 days or clear up and occur again within a few days
- you experience signs of skin injury such as pain, swelling, or blistering where the product was applied

PREGNANCY OR BREAST FEEDING

if pregnanat or breast feeding, ask a health professional before use.

keep out of reach of children and pets

if swallowed, get medical help or contact a Poison Control Center right away

INSTRUCTIONS FOR USE

Adult and children over 12years:

- Clean and dry affected area
- remove backing from patch by firmly grasping both ends and gently pulling until back separates in middle
- carefully remove smaller portion of backing from the patch and apply exposed portion of patch to affected area
- do not wear a patch for more than 8 hours
- apply affected area no more than 3 times daily

children 12 years or younger:

- ask a doctor

STORAGE AND HANDLING

Store at room temperature 20-25^0C (68-77^0F)

QUESTIONS

Call +91-905-677-0088

INACTIVE INGREDIENT

Alpha Tocopherol Acetate, Aluminium Glycinate, Aluminium Hydroxide, Aluminium Sulphate, Borax, Carbomer, Collodial Silicon Dioxide, DMDM Hydantoin, Glycerine, Kaolin, Polyacrylic Acid, Polyvinyl Alcohol, Polyvinylpyrrolidone, Propylene Glycol, Purified Water, Sodium Carboxymethyl Cellulose, Sodium Ethylenediaminetetraacetic Acid, Sodium Polyacrylate, Sorbitol, Sorbitan Monooleate, Tartaric Acid & Titanium Dioxide.

DOSAGE AND ADMINISTRATION

Topical Pain Relief Patch of External Use Only